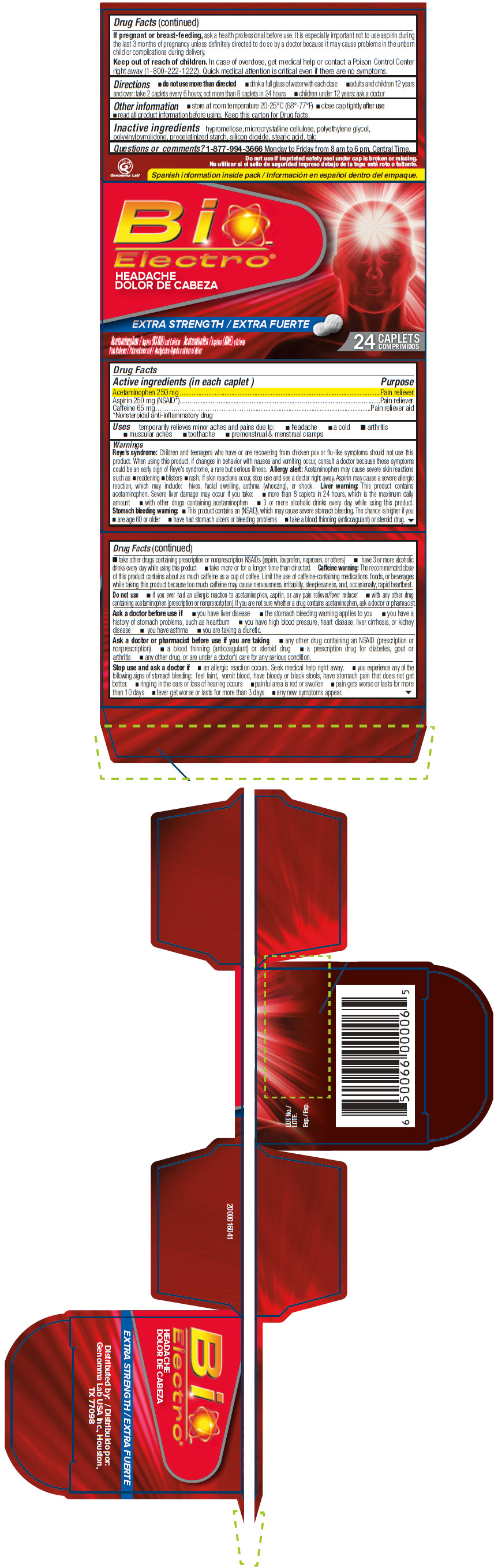 DRUG LABEL: BioElectro Extra Strength Headache Relief
NDC: 50066-630 | Form: TABLET
Manufacturer: Genomma Lab USA
Category: otc | Type: HUMAN OTC DRUG LABEL
Date: 20251230

ACTIVE INGREDIENTS: acetaminophen 250 mg/1 1; aspirin 250 mg/1 1; caffeine 65 mg/1 1
INACTIVE INGREDIENTS: HYPROMELLOSE, UNSPECIFIED; microcrystalline cellulose; POLYETHYLENE GLYCOL, UNSPECIFIED; POVIDONE K90; STARCH, CORN; silicon dioxide

BioElectro® Extra Strength Headache Relief

Drug Facts

ACTIVE INGREDIENT

Active ingredients (in each caplet) | Purpose
Acetaminophen 250 mg | Pain reliever
Aspirin 250 mg (NSAID [Nonsteroidal anti-inflammatory drug]) | Pain reliever
Caffeine 65 mg | Pain reliever aid

Uses

temporarily relieves minor aches and pains due to:

- headache
- a cold
- arthritis
- muscular aches
- toothache
- premenstrual & menstrual cramps

Warnings

Reye's syndrome

Children and teenagers who have or are recovering from chicken pox or flu-like symptoms should not use this product. When using this product, if changes in behavior with nausea and vomiting occur, consult a doctor because these symptoms could be an early sign of Reye's syndrome, a rare but serious illness.

Allergy alert

Acetaminophen may cause severe skin reactions such as

- reddening
- blisters
- rash.

If skin reactions occur, stop use and see a doctor right away. Aspirin may cause a severe allergic reaction, which may include: hives, facial swelling, asthma (wheezing), or shock.

Liver warning

This product contains acetaminophen. Severe liver damage may occur if you take:

- more than 8 caplets in 24 hours, which is the maximum daily amount
- with other drugs containing acetaminophen
- 3 or more alcoholic drinks every day while using this product.

Stomach bleeding warning

- This product contains an (NSAID), which may cause severe stomach bleeding. The chance is higher if you
  - are age 60 or older
  - have had stomach ulcers or bleeding problems
  - take a blood thinning (anticoagulant) or steroid drug.
  - take other drugs containing prescription or nonprescription NSAIDs (aspirin, ibuprofen, naproxen, or others)
  - have 3 or more alcoholic drinks every day while using this product
  - take more or for a longer time than directed.

Caffeine warning

The recommended dose of this product contains about as much caffeine as a cup of coffee. Limit the use of caffeine-containing medications, foods, or beverages while taking this product because too much caffeine may cause nervousness, irritability, sleeplessness, and, occasionally, rapid heartbeat.

Do not use

- if you ever had an allergic reaction to acetaminophen, aspirin, or any pain reliever/fever reducer
- with any other drug containing acetaminophen (prescription or nonprescription). If you are not sure whether a drug contains acetaminophen, ask a doctor or pharmacist.

Ask a doctor before use if

- you have liver disease
- the stomach bleeding warning applies to you
- you have a history of stomach problems, such as heartburn
- you have high blood pressure, heart disease, liver cirrhosis, or kidney disease
- you have asthma
- you are taking a diuretic.

Ask a doctor or pharmacist before use if you are taking

- any other drug containing an NSAID (prescription or nonprescription)
- a blood thinning (anticoagulant) or steroid drug
- a prescription drug for diabetes, gout or arthritis
- any other drug, or are under a doctor's care for any serious condition.

Stop use and ask a doctor if

- an allergic reaction occurs. Seek medical help right away.
- you experience any of the following signs of stomach bleeding: feel faint, vomit blood, have bloody or black stools, have stomach pain that does not get better.
- ringing in the ears or loss of hearing occurs
- painful area is red or swollen
- pain gets worse or lasts for more than 10 days
- fever get worse or lasts for more than 3 days
- any new symptoms appear.

PREGNANCY OR BREAST FEEDING

If pregnant or breast-feeding, ask a health professional before use. It is especially important not to use aspirin during the last 3 months of pregnancy unless definitely directed to do so by a doctor because it may cause problems in the unborn child or complications during delivery.

Keep out of reach of children. In case of overdose, get medical help or contact a Poison Control Center right away (1-800-222-1222). Quick medical attention is critical even if there are no symptoms.

Directions

- do not use more than directed
- drink a full glass of water with each dose
- adults and children 12 years and over: take 2 caplets every 6 hours; not more than 8 caplets in 24 hours
- children under 12 years: ask a doctor

Other information

- store at room temperature 20-25°C (68°-77°F)
- close cap tightly after use
- read all product information before using. Keep this carton for Drug facts.

Inactive ingredients

hypromellose, microcrystalline cellulose, polyethylene glycol, polyvinylpyrrolidone, pregelatinized starch, silicon dioxide, stearic acid, talc

Questions or comments?

1-877-994-3666 Monday to Friday from 8 am to 6 pm, Central Time.

Distributed by:
Genomma Lab USA Inc., Houston,
TX 77098

PRINCIPAL DISPLAY PANEL - 24 Caplet Bottle Carton

Bio
Electro®

HEADACHE

EXTRA STRENGTH

Acetaminophen / Aspirin (NSAID) and Caffeine
Pain Reliever / Pain reliever aid

24 CAPLETS